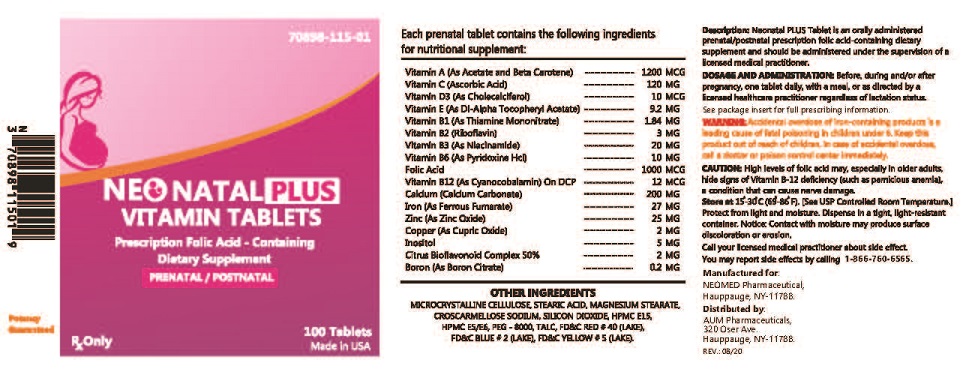 DRUG LABEL: NEONATAL PLUS VITAMIN
NDC: 70898-115 | Form: TABLET
Manufacturer: NEOMED PHARMACEUTICAL
Category: prescription | Type: HUMAN PRESCRIPTION DRUG LABEL
Date: 20200918

ACTIVE INGREDIENTS: VITAMIN A 1200 ug/1 1; ASCORBIC ACID 20 mg/1 1; CHOLECALCIFEROL 10 ug/1 1; .ALPHA.-TOCOPHEROL ACETATE 9.2 mg/1 1; THIAMINE 1.84 mg/1 1; RIBOFLAVIN 3 mg/1 1; NIACINAMIDE 20 mg/1 1; PYRIDOXINE HYDROCHLORIDE 10 mg/1 1; FOLIC ACID 1000 ug/1 1; CYANOCOBALAMIN 12 ug/1 1; FERROUS FUMARATE 27 mg/1 1; INOSITOL 5 mg/1 1; CITRUS BIOFLAVONOIDS 2 mg/1 1; CALCIUM 200 mg/1 1; BORON 0.2 mg/1 1; ZINC OXIDE 25 mg/1 1; COPPER 2 mg/1 1
INACTIVE INGREDIENTS: CROSCARMELLOSE SODIUM; MICROCRYSTALLINE CELLULOSE; CALCIUM PHOSPHATE, DIBASIC, ANHYDROUS; STEARIC ACID; SILICON DIOXIDE; TITANIUM DIOXIDE; MAGNESIUM STEARATE; TALC; POLYETHYLENE GLYCOL 8000; HYPROMELLOSES; TRIACETIN; SUCROSE; FD&C RED NO. 40; FD&C YELLOW NO. 6

NEONATAL PLUS VITAMIN
prenatal/postnatal multi-vitamin/mineral tablet
Rx

WARNING

Accidental overdose of iron-containing products is a leading cause of fatal poisoning in children under 6. KEEP THIS PRODUCT OUT OF THE REACH OF CHILDREN. In case of accidental overdose, call a doctor or poison control center immediately.

STATEMENT OF IDENTITY

Each prenatal tablet contains:

Each Tablet contains:
Vitamin A (as acetate, beta carotene) |  | 1200 mcg
Vitamin D3 (as cholecalciferol) |  | 10 mcg
Vitamin E (as dl-alpha topcopheryl acetate) |  | 9.2 mg
Vitamin C (Ascorbic acid) |  | 20 mg
Vitamin B1 (as thiamine HCl) |  | 1.84 mg
Vitamin B2 (as riboflavin) |  | 3 mg
Vitamin B3 (as niacinamide) |  | 20 mg
Vitamin B6 (as pyridoxine HCl) |  | 10 mg
Folic acid |  | 1000 mcg
Vitamin B12 (as cyanocobalamin) |  | 12 mcg
Iron (as ferrous fumarate) |  | 27 mg
Citrus bioflavonoids complex 50% bio flavonoids |  | 2 mg
Calcium (as carbonate sulfate) |  | 200 mg
Zinc (as zinc oxide) |  | 25 mg
Copper (as cupric oxide) |  | 2 mg
Boron (as boron citrate) |  | 0.2 mg
Inositol |  | 5 mg

Other Ingredients: , microcrystalline croscarmellose sodium, stearic acid, silicon dioxide, titanium dioxide (as color), polyethylene glycol, sucrose, magnesium stearate, talc,triacetin, HPMC E15,HPMC E5/E6,FD&C RED #40 (LAKES),FD&C YELLOW # 6 (LAKE)

INDICATIONS AND USAGE

NEONATAL PLUS TABLET Rx is a multi-vitamin/mineral prescription drug indicated for use in improving the nutritional status of women prior to conception, throughout pregnancy, and in the postnatal period for both lactating and nonlactating mothers.

CONTRAINDICATIONS

This product is contraindicated in patients with a known hypersensitivity to any of the ingredients.

WARNINGS

Folic acid alone is improper therapy in the treatment of pernicious anemia and other megaloblastic anemias where vitamin B12 is deficient.

PRECAUTIONS

Folic acid in doses above 0.1 mg daily may obscure pernicious anemia in that hematologic remission can occur while neurological manifestations progress.

ADVERSE REACTIONS

Allergic sensitization has been reported following both oral and parenteral administration of folic acid.

To report a serious adverse event or obtain product information, call 631-524-5758

DOSAGE AND ADMINISTRATION

One tablet daily or as directed by a physician.

HOW SUPPLIED

Bottles of 100 tablets each - NDC 70898-115-01

STORAGE

Store at 20-25°C (68-77°F) [See USP controlled room temperature].

To report a serious adverse event or obtain product information, call 631-524-5758

Distributed by:

Neomed Pharmaceutical ,80 Cain Dr, Brentwood,NY 11717

Phone :631-524-5758

Email: info@neomedpharmaceutical.com